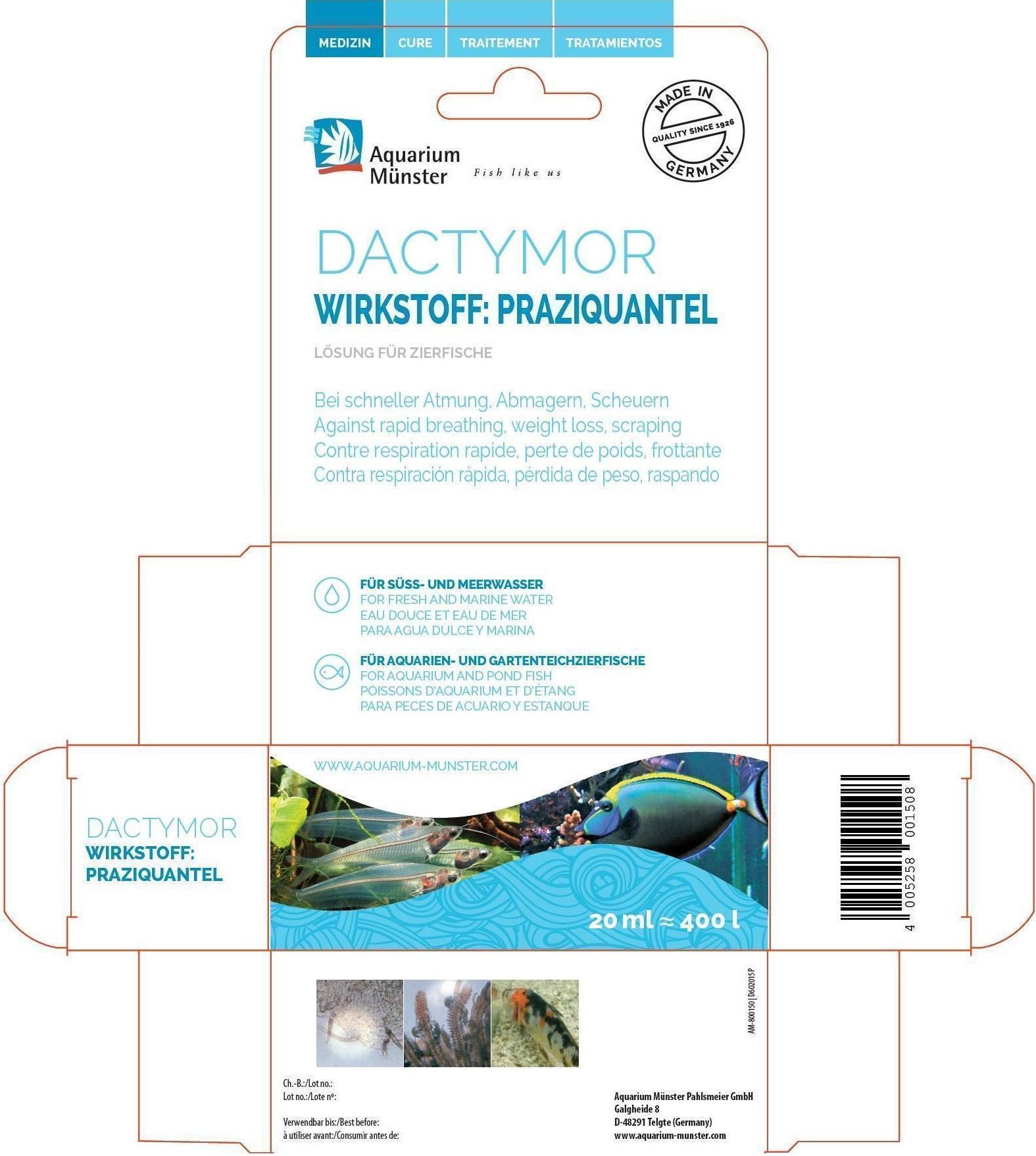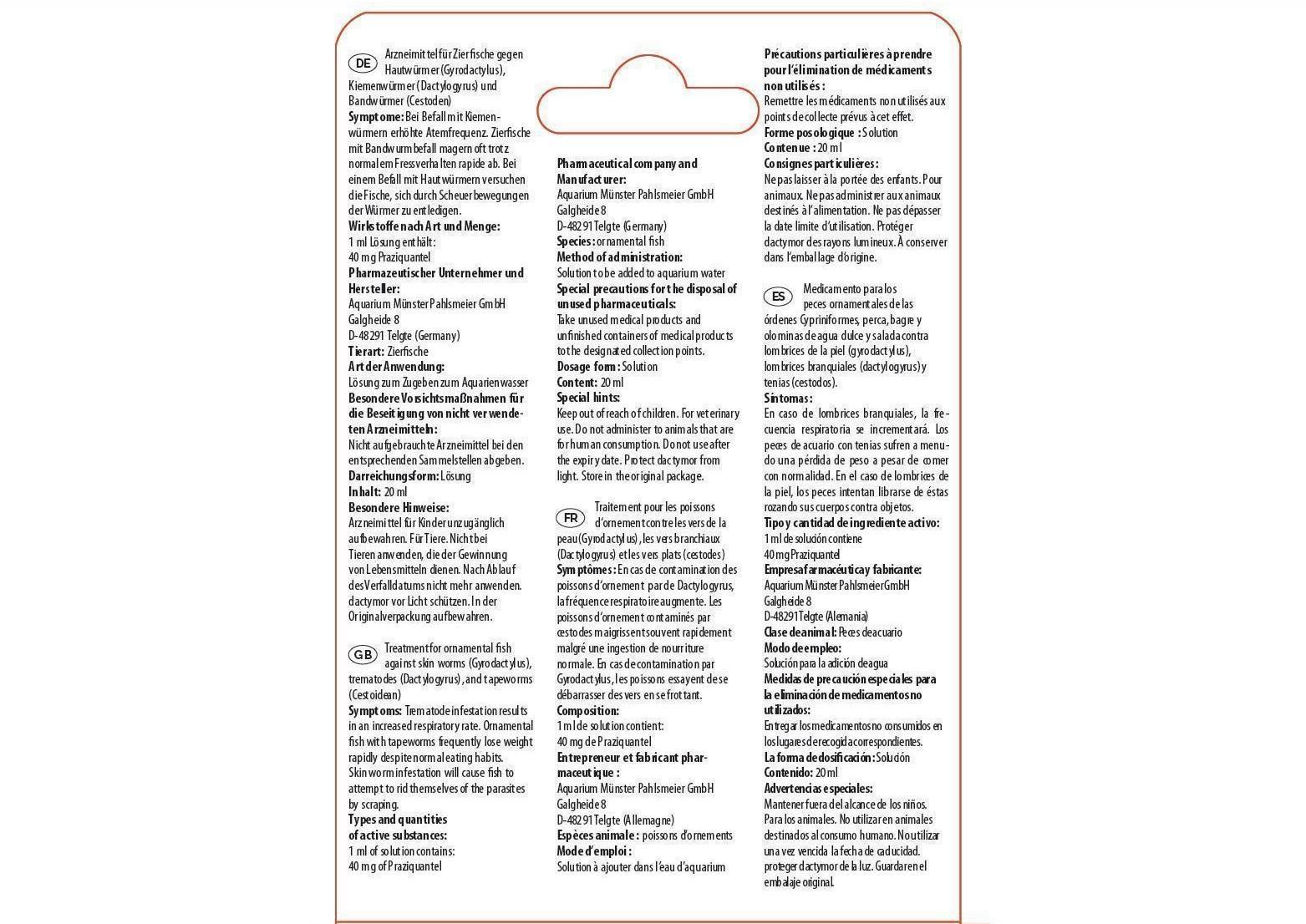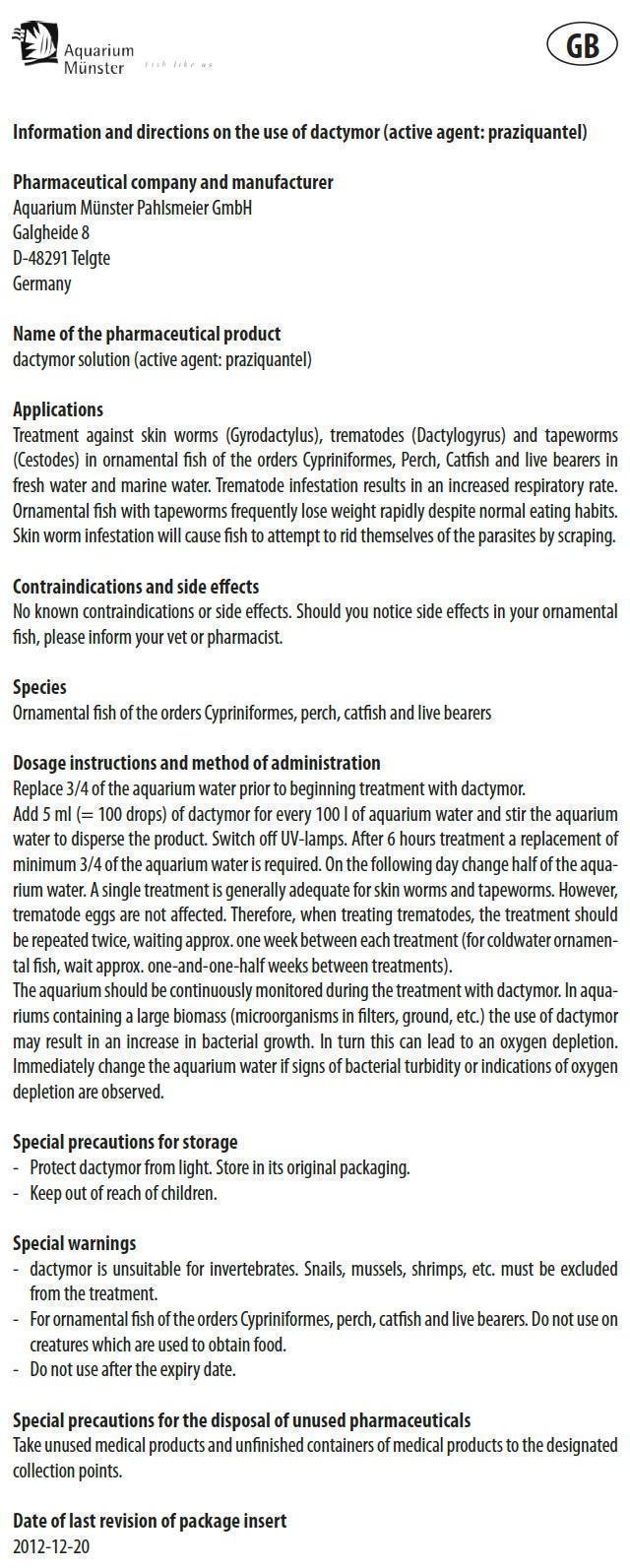 DRUG LABEL: DACTYMOR
NDC: 86052-002 | Form: SOLUTION
Manufacturer: Aquarium Muenster Pahlsmeier GmbH
Category: animal | Type: OTC ANIMAL DRUG LABEL
Date: 20240419

ACTIVE INGREDIENTS: PRAZIQUANTEL 10 mg/1 mL

DACTYMOR

Information and directions on the use of dactymor (active agent: praziquantel)

Pharmaceutical company and manufacturer
Aquarium Münster Pahlsmeier GmbH
Galgheide 8
D-48291 Telgte
Germany
Name of the pharmaceutical product
dactymor solution (active agent: praziquantel)

Applications

Treatment against skin worms (Gyrodactylus), trematodes (Dactylogyrus) and tapeworms (Cestodes) in ornamental fish of the orders Cypriniformes, Perch, Catfish and live bearers in fresh water and marine water. Trematode infestation results in an increased respiratory rate. Ornamental fish with tapeworms frequently lose weight rapidly despite normal eating habits. Skin worm infestation will cause fish to attempt to rid themselves of the parasites by scraping.

Types and quantities of active substances:

1 ml of solution contains:

40 mg of Praziquantel

Contraindications and side effects

No known contraindications or side effects. Should you notice side effects in your ornamental fish, please inform your vet or pharmacist.

Species

Ornamental fish of the orders Cypriniformes, perch, catfish and live bearers

Dosage instructions and method of administration

Replace 3/4 of the aquarium water prior to beginning treatment with dactymor. Add 5 ml (= 100 drops) of dactymor for every 100 l of aquarium water and stir the aquarium water to disperse the product. Switch off UV-lamps. After 6 hours treatment a replacement of minimum 3/4 of the aquarium water is required. On the following day change half of the aquarium water. A single treatment is generally adequate for skin worms and tapeworms. However, trematode eggs are not affected. Therefore, when treating trematodes, the treatment should be repeated twice, waiting approx. one week between each treatment (for coldwater ornamental fish, wait approx. one-and-one-half weeks between treatments).
The aquarium should be continuously monitored during the treatment with dactymor. In aquariums containing a large biomass (microorganisms in filters, ground, etc.) the use of dactymor may result in an increase in bacterial growth. In turn this can lead to an oxygen depletion. Immediately change the aquarium water if signs of bacterial turbidity or indications of oxygen depletion are observed.

Special precautions for storage

- Protect dactymor from light. Store in its original packaging.

- Keep out of reach of children.

Special Warnings

- dactymor is unsuitable for invertebrates. Snails, mussels, shrimps, etc. must be excluded from the treatment.
- For ornamental fish of the orders Cypriniformes, perch, catfish and live bearers. Do not use on creatures which are used to obtain food.
- Do not use after the expiry date.

DO NOT USE

For veterinary use. Do not administer to animals that are for human consumption. Do not use after the expiry date. Protect dactymor from light. Store in the original package.

Special precautions for the disposal of unused pharmaceuticals

Take unused medical products and unfinished containers of medical products to the designated collection points.

Date of last revision of package insert
2012-12-20